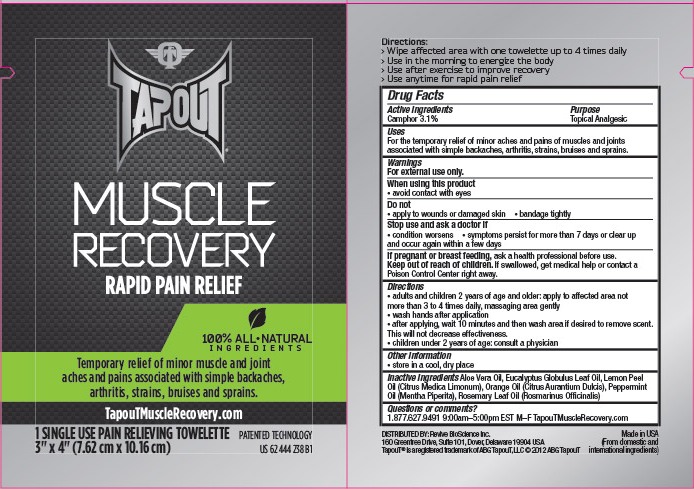 DRUG LABEL: TapouT
NDC: 76433-003 | Form: CLOTH
Manufacturer: Revive Bioscience, Inc.
Category: otc | Type: HUMAN OTC DRUG LABEL
Date: 20120126

ACTIVE INGREDIENTS: CAMPHOR (SYNTHETIC) 1 mL/1 1
INACTIVE INGREDIENTS: EUCALYPTUS OIL; LEMON OIL; ORANGE OIL; PEPPERMINT OIL; ROSEMARY OIL

ACTIVE INGREDIENT

camphor 3.1%

PURPOSE

Topical Analgesic

INDICATIONS AND USAGE

For the temporary relief of minor aches and pains of muscles and joints associated with simple backaches, arthritis, strains, bruises and sprains.

WARNINGS

For external use only.

When using this product

- avoid contact with eyes

Do not

- apply to wounds or damaged skin
- bandage tightly

Stop use and ask a doctor if

- condition worsens
- symptoms persist for more than 7 days or clear up and occur again within a few days

PREGNANCY OR BREAST FEEDING

If pregnant or breast feeding, ask a health professional before use.

Keep out of reach of children. If swallowed, get medical help or contact a Poison Control Center right away.

Directions

- adults and children 2 years of age and older: apply to affected area not more than 3 to 4 times daily, massaging area gently
- wash hands after application
- after applying, wait 10 minutes and then wash area if desired to remove scent. This will not decrease effectiveness.
- children under 2 years of age: consult a physician

STORAGE AND HANDLING

store in a cool, dry place

INACTIVE INGREDIENT

Aloe Vera Oil, Eucalyptus Globulus Leaf Oil, Lemon Peel Oil (Citrus Medica Limonum), Orange Oil (Citrus Aurantium Dulcis), Peppermint Oil (Mentha Piperita), Rosemary Leaf Oil (Rosmarinus Officinalis)

Questions or comments?

1.877.627.9491 9:00am-5:00pm EST M-F

TapouTMuscleRecovery.com